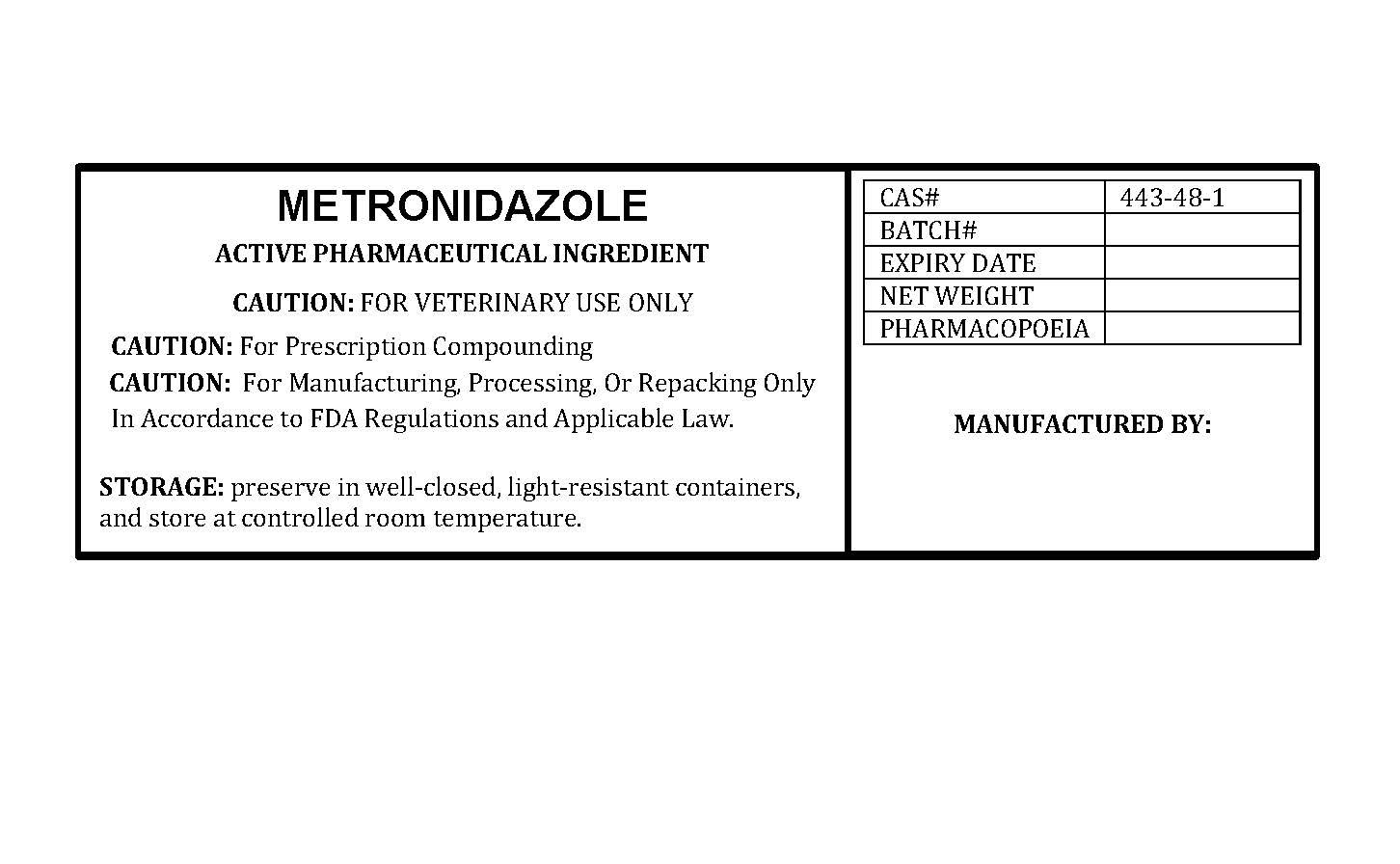 DRUG LABEL: METRONIDAZOLE
NDC: 86184-255 | Form: POWDER
Manufacturer: MAEDA INC
Category: other | Type: BULK INGREDIENT - ANIMAL DRUG
Date: 20260213

ACTIVE INGREDIENTS: METRONIDAZOLE 1 g/1 g

METRONIDAZOLE

PACKAGE LABEL

metronidazolabelfile.jpg